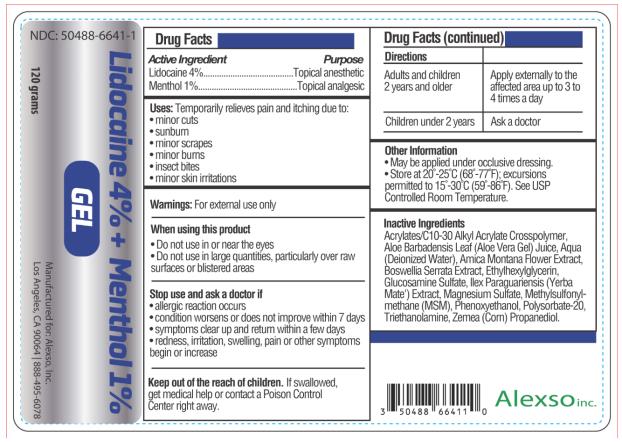 DRUG LABEL: Lidocaine and Menthol
NDC: 50488-6641 | Form: GEL
Manufacturer: Alexso, Inc
Category: otc | Type: HUMAN OTC DRUG LABEL
Date: 20210217

ACTIVE INGREDIENTS: LIDOCAINE 4.8 g/120 g; MENTHOL 1.2 g/120 g
INACTIVE INGREDIENTS: CARBOMER INTERPOLYMER TYPE A (55000 CPS); ALOE VERA LEAF; WATER; ARNICA MONTANA FLOWER; INDIAN FRANKINCENSE; ETHYLHEXYLGLYCERIN; GLUCOSAMINE SULFATE; ILEX PARAGUARIENSIS LEAF; MAGNESIUM SULFATE, UNSPECIFIED; DIMETHYL SULFONE; PHENOXYETHANOL; POLYSORBATE 20; TROLAMINE; CORN

Lidocaine and Menthol Gel

LIDOCAINE AND MENTHOL - Lidocaine 4% and Menthol 1% Gel
Alexso, Inc

Disclaimer: Most OTC drugs are not reviewed and approved by FDA, however they may be marketed if they comply with applicable regulations and policies. FDA has not evaluated whether this product complies.

----------

Lidocaine 4% and Menthol 1% Gel

Drug Facts

Purpose

Lidocaine 4% ………………………..Topical anesthetic
Menthol 1% …………………………Topical analgesic

Uses

Temporarily relieves pain and itching due to:

- minor cuts
- sunburn
- minor scrapes
- minor burns
- insect bites
- minor skin irritations

Warnings

For external use only.

When using this product

- do not use in or near the eyes
- do not use in large quantities, particularly over raw surfaces or blistered areas
- do not apply to wounds or damaged skin
- do not bandage

Stop use and ask a doctor if

- allergic reaction occurs
- condition worsens or does not improve within 7 days
- symptoms clear up and return within a few days
- redness, irritation, swelling, pain or other symptoms begin or increase

Keep out of reach of children.

If swallowed, get medical help or contact a Poison Control Center right away.

Directions

adults and children 2 years and older | apply externally to the affected area up to 3 to 4 times a day
children under 2 years | do not use except under the advice and supervision of a physician

Other information

- May be applied under occlusive dressing.
- Store at 20-25°C (68-77°F); excursions permitted to 15-30°C (59-86°F). See USP Controlled Room Temperature.

Inactive ingredients

Acrylates/C10-30 Alkyl Acrylate Crosspolymer, Aloe Barbadensis Leaf (Aloe Vera Gel) Juice, Aqua (Deionized Water), Arnica Montana Flower Extract, Boswellia Serrata Extract, Ethylhexylglycerin, Glucosamine Sulfate, Ilex Paraguariensis (Yerba Mate’) Extract, Magnesium Sulfate, Methylsulfonylmethane (MSM), Phenoxyethanol, Polysorbate-20, Triethanolamine, Zemea (Corn) Propanediol

Lidocaine 4% and Menthol 1% Gel

NDC 50488-6641-1

120 grams

Manufactured for:
Alexso, Inc.
Los Angeles, CA 90064

PRINCIPAL DISPLAY PANEL

NDC 50488-6641-1
Lidocaine 4% + Menthol 1%
120 grams